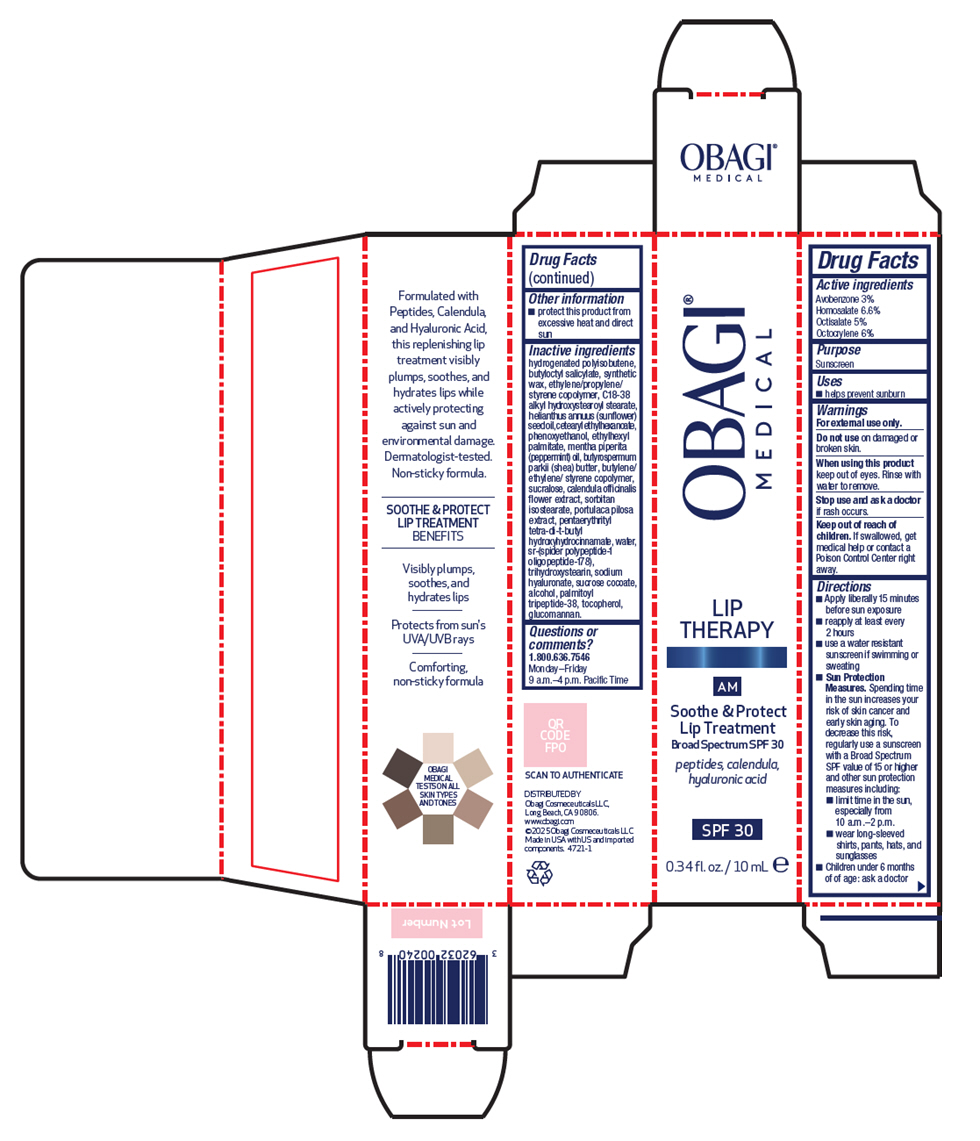 DRUG LABEL: Lip Therapy Soothe and Protect Lip Treatment Broad Spectrum SPF 30
NDC: 62032-926 | Form: GEL
Manufacturer: Obagi Cosmeceuticals LLC
Category: otc | Type: HUMAN OTC DRUG LABEL
Date: 20250819

ACTIVE INGREDIENTS: Avobenzone 3 mg/100 mL; Homosalate 6.6 mg/100 mL; Octisalate 5 mg/100 mL; Octocrylene 6 mg/100 mL
INACTIVE INGREDIENTS: Butyloctyl Salicylate; C18-38 Alkyl Hydroxystearoyl Stearate; SUNFLOWER OIL; Cetearyl Ethylhexanoate; Phenoxyethanol; Ethylhexyl Palmitate; PEPPERMINT OIL; SHEA BUTTER; Sucralose; CALENDULA OFFICINALIS FLOWER; Sorbitan Isostearate; PENTAERYTHRITOL TETRAKIS(3-(3,5-DI-TERT-BUTYL-4-HYDROXYPHENYL)PROPIONATE); Water; Trihydroxystearin; HYALURONATE SODIUM; Sucrose Cocoate; Alcohol; Palmitoyl Tripeptide-38; Tocopherol; KONJAC MANNAN

Lip Therapy Soothe & Protect Lip Treatment Broad Spectrum SPF 30

Drug Facts

Active ingredients

Avobenzone 3%
Homosalate 6.6%
Octisalate 5%
Octocrylene 6%

Purpose

Sunscreen

Uses

- helps prevent sunburn

Warnings

For external use only.

Do not use on damaged or broken skin.

When using this product keep out of eyes. Rinse with water to remove.

Stop use and ask a doctor if rash occurs.

Keep out of reach of children. If swallowed, get medical help or contact a Poison Control Center right away.

Directions

- Apply liberally 15 minutes before sun exposure
- reapply at least every 2 hours
- use a water resistant sunscreen if swimming or sweating
- Sun Protection Measures. Spending time in the sun increases your risk of skin cancer and early skin aging. To decrease this risk, regularly use a sunscreen with a Broad Spectrum SPF value of 15 or higher and other sun protection measures including:
  - limit time in the sun, especially from 10 a.m.–2 p.m.
  - wear long-sleeved shirts, pants, hats, and sunglasses
- Children under 6 months of of age: ask a doctor

Other information

- protect this product from excessive heat and direct sun

Inactive ingredients

hydrogenated polyisobutene, butyloctyl salicylate, synthetic wax, ethylene/propylene/styrene copolymer, C18-38 alkyl hydroxystearoyl stearate, helianthus annuus (sunflower) seed oil, cetearyl ethylhexanoate, phenoxyethanol, ethylhexyl palmitate, mentha piperita (peppermint) oil, butyrospermum parkii (shea) butter, butylene/ethylene/ styrene copolymer, sucralose, calendula officinalis flower extract, sorbitan isostearate, portulaca pilosa extract, pentaerythrityl tetra-di-t-butyl hydroxyhydrocinnamate, water, sr-(spider polypeptide-1 oligopeptide-178), trihydroxystearin, sodium hyaluronate, sucrose cocoate, alcohol, palmitoyl tripeptide-38, tocopherol, glucomannan.

Questions or comments?

1.800.636.7546
Monday–Friday
9 a.m.–4 p.m. Pacific Time

DISTRIBUTED BY
Obagi Cosmeceuticals LLC,
Long Beach, CA 90806.

PRINCIPAL DISPLAY PANEL - 10 mL Tube Carton

OBAGI®
MEDICAL

LIP
THERAPY

AM

Soothe & Protect
Lip Treatment
Broad Spectrum SPF 30

peptides, calendula,
hyaluronic acid

SPF 30

0.34 fl. oz. / 10 mL ℮